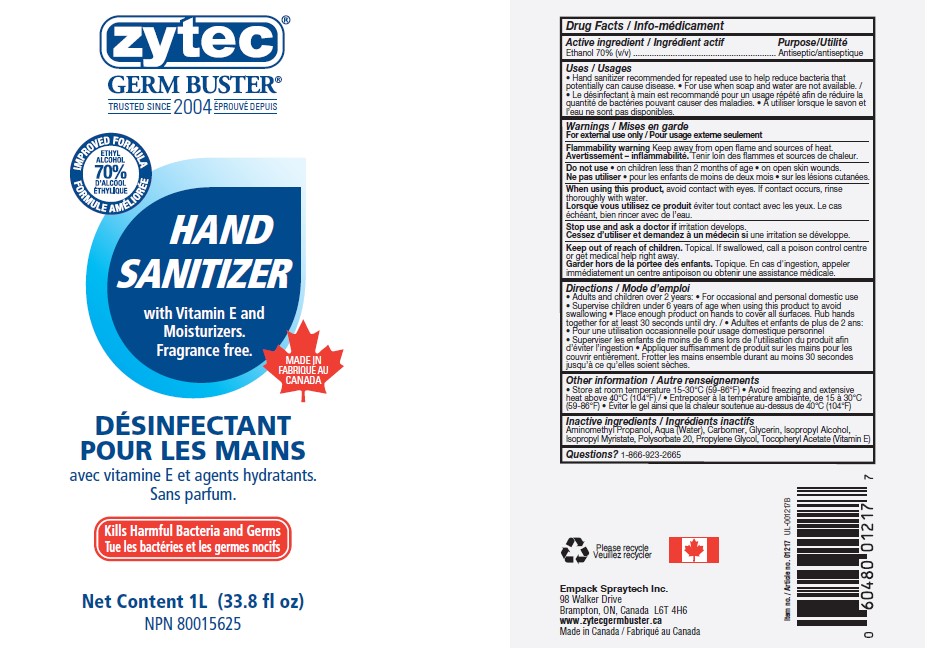 DRUG LABEL: Hand Sanitizer
NDC: 50021-009 | Form: GEL
Manufacturer: Empack Spraytech Inc.
Category: otc | Type: HUMAN OTC DRUG LABEL
Date: 20240920

ACTIVE INGREDIENTS: ALCOHOL 70 mL/100 mL
INACTIVE INGREDIENTS: WATER; ALOE VERA FLOWER; GLYCERIN; AMINOMETHYLPROPANOL; CARBOMER 940; ISOPROPYL ALCOHOL; ISOPROPYL MYRISTATE; POLYSORBATE 20; PROPYLENE GLYCOL; .ALPHA.-TOCOPHEROL ACETATE, DL-

50021-009 Hand Sanitizer

Active Ingredients (v/v)

Ethyl Alcohol 70%

Purpose

Antiseptic

Uses

Hand Sanitizer to help reduces bacteria that potentially can cause disease. Recommended for repeated use. For use when soap and

water are not available

Warnings

For external use only. Flammable. Keep away from fire or flame

Do not use

- in children less than 2 months age

- on open skin wounds

Stop use and ask a doctorif rash occurs.

WHEN USING

When using this productkeep out of eyes, ears, and mouth. in case of contact with eyes, rinse with water

Keep out of reach of children.If swallowed, get medical help or contact a Poison Control Center right away.

Directions

• Place enough product on hands to cover all surfaces. Rub hands together until dry

• Supervise children under 6 years of age when using this product to avoid swallowing

Other Information

- Store at room temperature 15-30 C (59-86°F).

- Avoid freezing and extrensive heat avbove 40C (104F)

Inactive Ingredients

Aloe Barbadensis Leaf Juice, Aminomethyl Propanol, Aqua (Water), Carbomer, Glycerin, lsopropyl Alcohol, lsopropyl Myristate, Parfum (Fragrance), Polysorbate 20, Propylene Glycol, Tocopheryl Acetate (Vitamin E), Blue 1, Red 40, Yellow 5

Questions ?

1-866-923-2665

Manufactured in Canada by Empack Spraytech Inc., 98 Walker Drive, Brampton, ON, L6T 4H6

UPC Please recycle (+ logo) Lot # and Expiry Date to be embossed on the tube seal

Principal Display Panel

Zytec Germ Buster Hand Sanitizer Gel

Alcohol Antiseptic 70%

Packge size ranges between 100 ml to 1 Gal